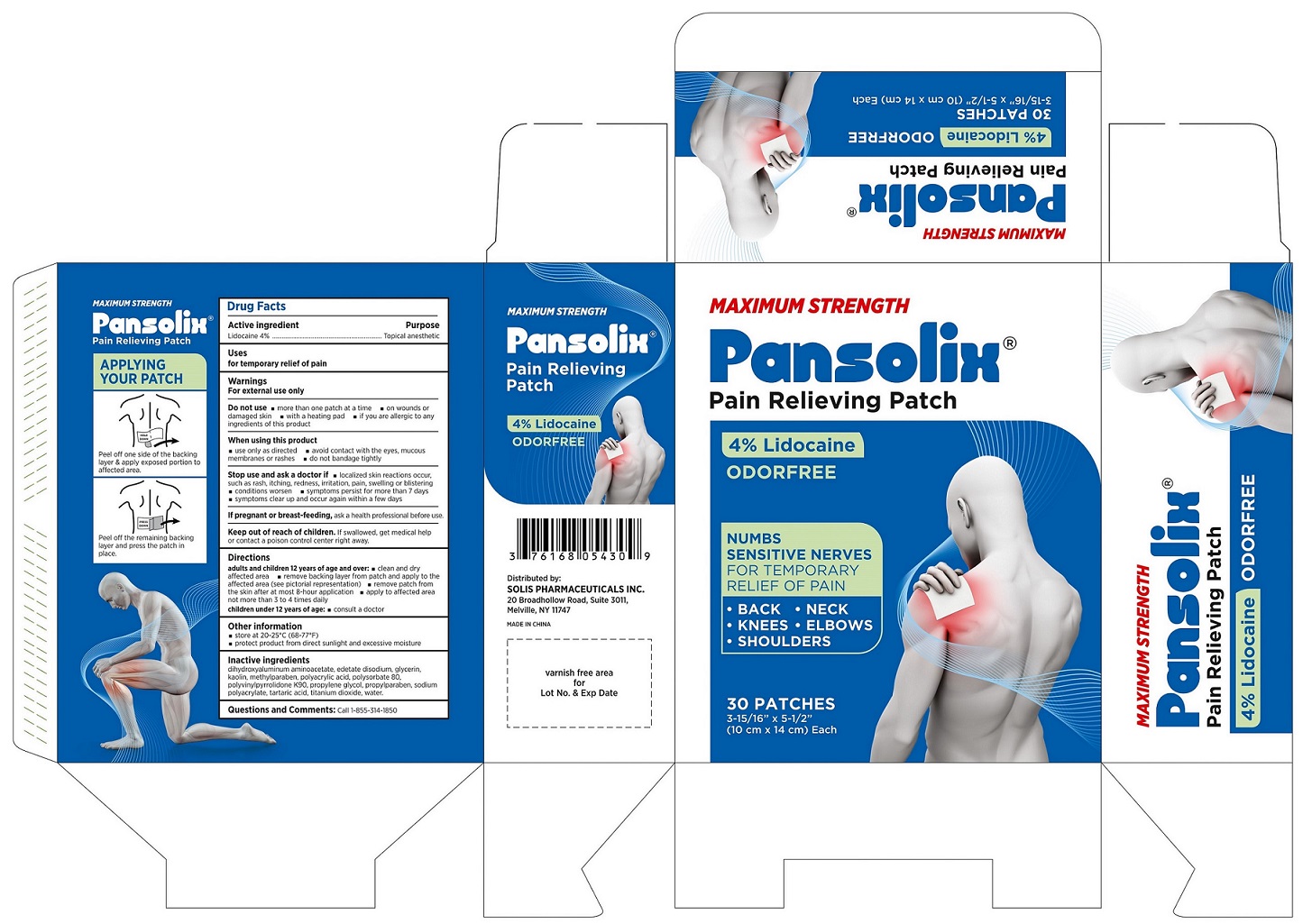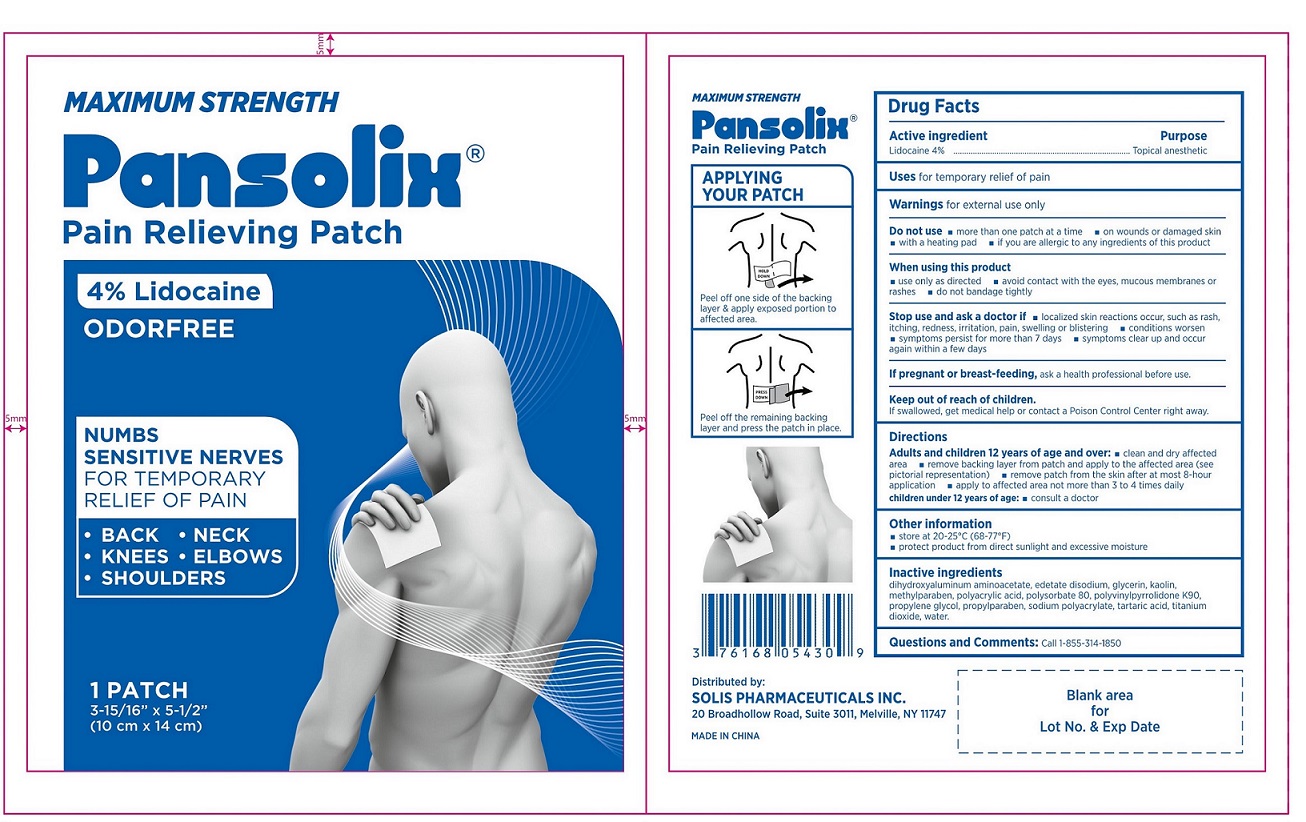 DRUG LABEL: Maximum Strength 4% Lidocaine Patch
NDC: 85185-001 | Form: PATCH
Manufacturer: Solis Pharmaceuticals Inc.
Category: otc | Type: HUMAN OTC DRUG LABEL
Date: 20250429

ACTIVE INGREDIENTS: LIDOCAINE 40 mg/1 1
INACTIVE INGREDIENTS: POVIDONE K90; POLYSORBATE 80; TARTARIC ACID; TITANIUM DIOXIDE; POLYACRYLIC ACID (250000 MW); DIHYDROXYALUMINUM AMINOACETATE; GLYCERIN; EDETATE DISODIUM ANHYDROUS; METHYLPARABEN; SODIUM POLYACRYLATE (2500000 MW); PROPYLENE GLYCOL; KAOLIN; PROPYLPARABEN; WATER

Maximum Strength 4% Lidocaine Patch

Active Ingredient

Lidocaine 4%

Purpose

Topical Anesthetic

Uses

for temporary relief of pain

Warnings

For external use only

Do Not Use

- more than one patch at a time
- on wounds or damaged skin
- with a heating pad
- if you are allergic to any ingredients of this product

When Using This Product

- use only as directed rashes
- avoid contact with the eyes, mucous membranes or rashes
- do not bandage tightly

Stop Use and Ask a Doctor if

- localized skin reactions occur, such as rash, itching, redness, irritation, pain, swelling or blistering
- conditions worsen
- symptoms persist for more than 7 days
- symptoms clear up and occur again within a few days

If Pregnant or Breast Feeding

ask a health professional before use.

Keep Out of Reach of Children and Pets

If swallowed, get medical help or contact a Poison Control Center right away.

Directions

Adults and children 12 years of age and over:

- clean and dry affected area
- remove backing layer from patch and apply to the affected area (see pictorial representation)
- remove patch from the skin after at most 8-hour application
- apply to affected area not more than 3 to 4 times daily

children under 12 years of age: consult a doctor

Other information

- store at 20-25°C (68-77°F)
- protect product from direct sunlight and excessive moisture

Inactive Ingredients

dihydroxyaluminum aminoacetate, edetate disodium, glycerin, kaolin, methylparaben, polyacrylic acid, polysorbate 80, polyvinylpyrrolidone K90, propylene glycol, propylparaben, sodium polyacrylate, tartaric acid, titanium dioxide, water.

Questions and Comments

Call 1-855-314-1850

Bulk Package Label

MAXIMUM STRENGTH
Pansolix® Pain Relieving Patch
4% Lidocaine
ODORFREE
NUMBS SENSITIVE NERVES FOR TEMPORARY RELIEF OF PAIN

- BACK NECK
- KNEES
- ELBOWS
- SHOULDERS

30 PATCHES 3-15/16" x 5-1/2" (10 cm x 14 cm)